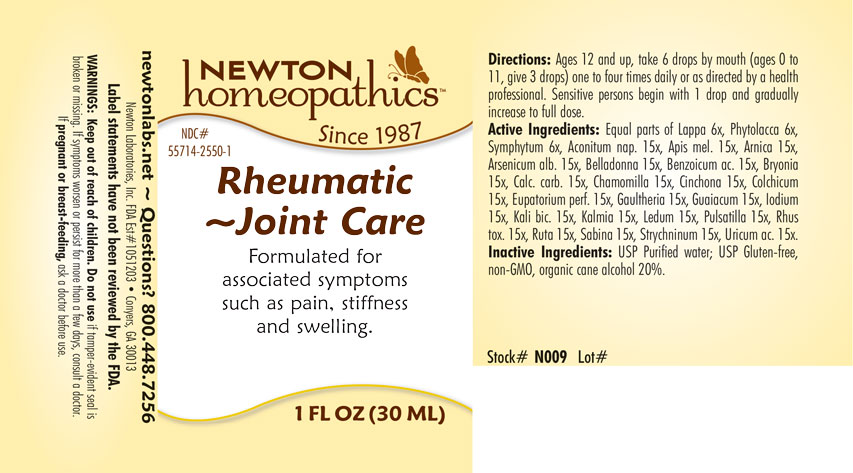 DRUG LABEL: Rheumatic-Joint Care
NDC: 55714-2550 | Form: LIQUID
Manufacturer: Newton Laboratories, Inc.
Category: homeopathic | Type: HUMAN OTC DRUG LABEL
Date: 20250723

ACTIVE INGREDIENTS: URIC ACID 15 [hp_X]/1 mL; ACONITUM NAPELLUS 15 [hp_X]/1 mL; APIS MELLIFERA 15 [hp_X]/1 mL; ARNICA MONTANA 15 [hp_X]/1 mL; ARSENIC TRIOXIDE 15 [hp_X]/1 mL; ATROPA BELLADONNA 15 [hp_X]/1 mL; BENZOIC ACID 15 [hp_X]/1 mL; BRYONIA ALBA ROOT 15 [hp_X]/1 mL; OYSTER SHELL CALCIUM CARBONATE, CRUDE 15 [hp_X]/1 mL; CINCHONA OFFICINALIS BARK 15 [hp_X]/1 mL; COLCHICUM AUTUMNALE BULB 15 [hp_X]/1 mL; EUPATORIUM PERFOLIATUM FLOWERING TOP 15 [hp_X]/1 mL; GAULTHERIA PROCUMBENS TOP 15 [hp_X]/1 mL; GUAIACUM OFFICINALE RESIN 15 [hp_X]/1 mL; IODINE 15 [hp_X]/1 mL; POTASSIUM DICHROMATE 15 [hp_X]/1 mL; KALMIA LATIFOLIA LEAF 15 [hp_X]/1 mL; RHODODENDRON TOMENTOSUM LEAFY TWIG 15 [hp_X]/1 mL; ANEMONE PULSATILLA 15 [hp_X]/1 mL; TOXICODENDRON PUBESCENS LEAF 15 [hp_X]/1 mL; RUTA GRAVEOLENS FLOWERING TOP 15 [hp_X]/1 mL; JUNIPERUS SABINA LEAFY TWIG 15 [hp_X]/1 mL; STRYCHNINE 15 [hp_X]/1 mL; ARCTIUM LAPPA ROOT 6 [hp_X]/1 mL; PHYTOLACCA AMERICANA ROOT 6 [hp_X]/1 mL; COMFREY ROOT 6 [hp_X]/1 mL; MATRICARIA CHAMOMILLA 15 [hp_X]/1 mL
INACTIVE INGREDIENTS: ALCOHOL; WATER

Rheumatic 2550L

INDICATIONS & USAGE SECTION

Formulated for associated symptoms such as pain, stiffness and swelling.

DOSAGE & ADMINISTRATION SECTION

Directions: Ages 12 and up, take 6 drops by mouth (ages 0 to 11, give 3 drops) one to four times daily or as directed by a health professional. Sensitive persons begin with 1 drop and gradually increase to full dose.

OTC - ACTIVE INGREDIENT SECTION

Equal parts of Lappa 6x, Phytolacca 6x, Symphytum 6x, Aconitum nap. 15x, Apis mel. 15x, Arnica 15x, Arsenicum alb. 15x, Belladonna 15x, Benzoicum acidum 15x, Bryonia 15x, Calc. carb. 15x, Chamomilla 15x, Cinchona 15x, Colchicum 15x, Eupatorium perf. 15x, Gaultheria 15x, Guaiacum 15x, Iodium 15x, Kali bic. 15x, Kalmia 15x, Ledum 15x, Pulsatilla 15x, Rhus toxicodendron 15x, Ruta 15x, Sabina 15x, Strychninum 15x, Uricum acidum 15x.

OTC - PURPOSE SECTION

Formulated for associated symptoms such as pain, stiffness and swelling.

INACTIVE INGREDIENT SECTION

Inactive Ingredients: USP Purified Water; USP Gluten-free, non-GMO, organic cane alcohol 20%

QUESTIONS SECTION

newtonlabs.net - Questions? 800.448.7256

Newton Laboratories, Inc. FDA Est # 1051203 Conyers, GA 30013

WARNINGS SECTION

WARNINGS: Keep out of reach of children. Do not use if tamper-evident seal is broken or missing. If symptoms worsen or persist for more than a few days, consult a doctor. If pregnant or breast-feeding, ask a doctor before use.

OTC - PREGNANCY OR BREAST FEEDING SECTION

If pregnant or breast-feeding, ask a doctor before use.

OTC - KEEP OUT OF REACH OF CHILDREN SECTION

Keep out of reach of children.